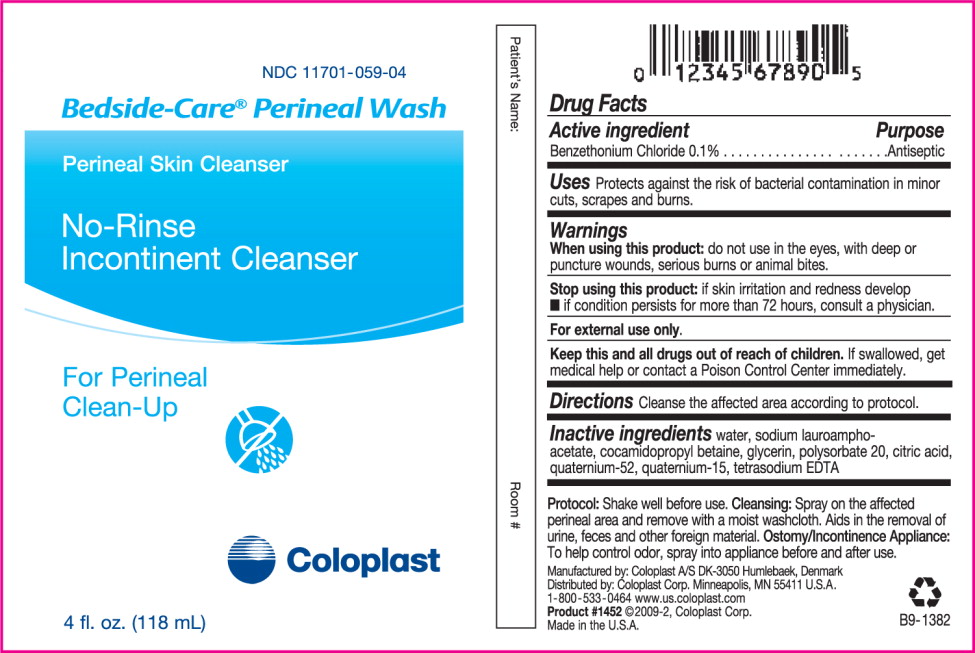 DRUG LABEL: Bedside-Care Perineal Wash
								
NDC: 11701-059 | Form: LIQUID
Manufacturer: Coloplast Manufacturing US, LLC
Category: otc | Type: HUMAN OTC DRUG LABEL
Date: 20110630

ACTIVE INGREDIENTS: BENZETHONIUM CHLORIDE 1 mL/1 L
INACTIVE INGREDIENTS: CITRIC ACID; EDETATE SODIUM; QUATERNIUM-15; GLYCERIN; QUATERNIUM-52; POLYSORBATE 20; COCAMIDOPROPYL BETAINE; SODIUM LAUROAMPHOACETATE; WATER

Bedside-Care® Perineal Wash
Perineal Skin Cleanser
No-Rinse
Incontinent Cleanser

For Perineal Clean-Up

Drug Facts

Active ingredient

Benzethonium Chloride 0.1%

Purpose

Antiseptic

INDICATIONS AND USAGE

Uses Protects against the risk of bacterial contamination in minor cuts, scrapes and burns.

Warnings

When using this product: do not use in the eyes, with deep or puncture wounds, serious burns or animal bites.

Stop using this product:

- if skin irritation and redness develop
- if condition persists for more than 72 hours, consult a physician.

For external use only.

KEEP OUT OF REACH OF CHILDREN

Keep this and all drugs out of the reach of children. If swallowed, get medical help or contact a Poison Control Center immediately.

DOSAGE AND ADMINISTRATION

Directions Cleanse the affected area according to protocol.

INACTIVE INGREDIENT

Inactive ingredients water, sodium lauroamphoacetate, cocamidopropyl betaine, glycerin, polysorbate 20, citric acid, quaternium-52, quaternium-15, tetrasodium EDTA

Protocol: Shake well before use. Cleansing: Spray on the affected perineal area and remove with a moist washcloth. Aids in the removal of urine, feces and other foreign material. Ostomy/Incontinence Appliance: To help control odor, spray into appliance before and after use.

Manufactured by: Coloplast A/S
DK-3050 Humlebaek, Denmark
Distributed by: Coloplast Corp.
Minneapolis, MN 55411 U.S.A.
1-800-533-0464 www.us.coloplast.com
Product #1453 ©2009-2, Coloplast Corp.
Made in the U.S.A.

B9-1383

PACKAGE LABEL

PRINCIPAL DISPLAY PANEL - NET WT. 8 fl. oz. (237mL)

NDC 11701-059-05

Bedside-Care® Perineal Wash

Perineal Skin Cleanser

No-Rinse

Incontinent Cleanser

For Perineal Clean-Up

Coloplast

NET WT. 8 fl. oz. (237mL)